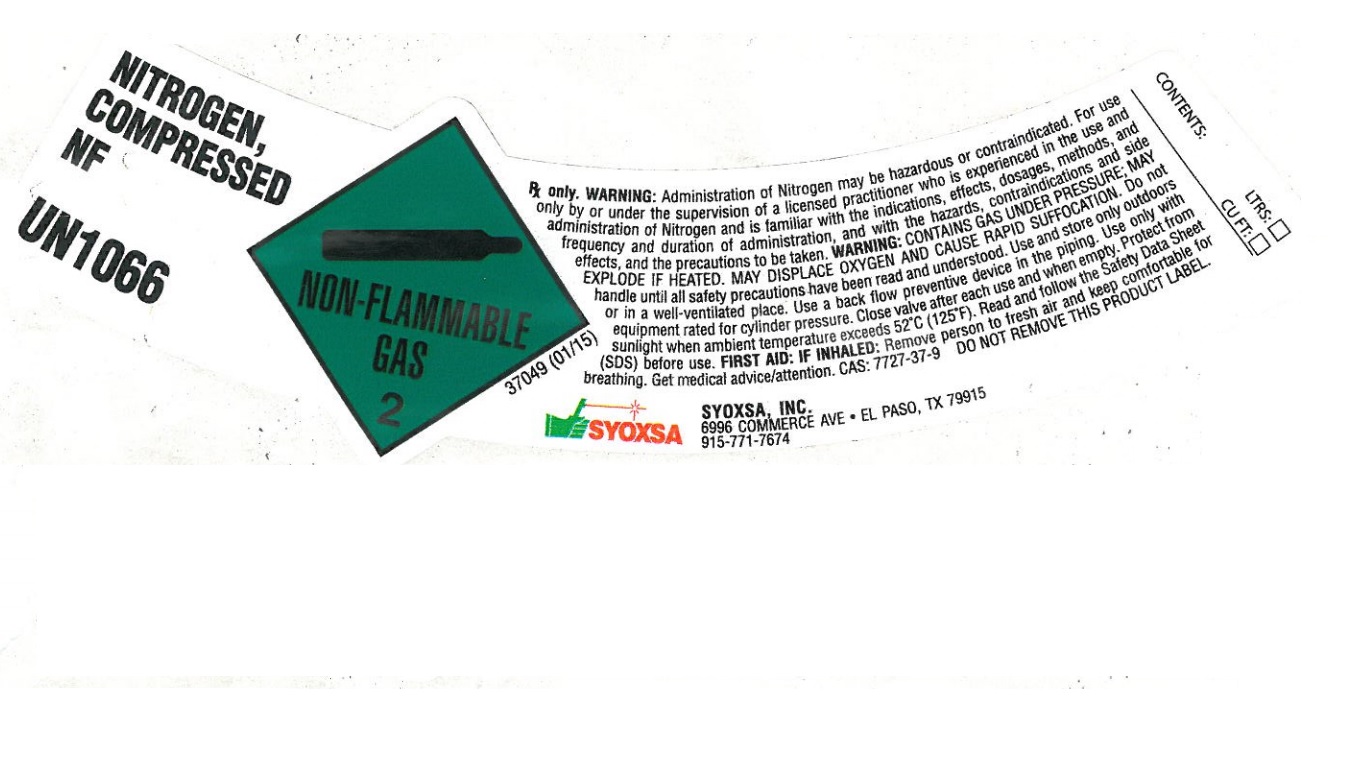 DRUG LABEL: Nitrogen
NDC: 23647-012 | Form: GAS
Manufacturer: SYOXSA, Inc.
Category: animal | Type: PRESCRIPTION ANIMAL DRUG LABEL
Date: 20251212

ACTIVE INGREDIENTS: NITROGEN 990 mL/1 L

Nitrogen

PACKAGE LABEL

NITROGEN, COMPRESSED NF
UN1066
RX only. WARNING: Administration of Nitrogen may be hazardous or contraindicated. For use only by or under the supervision of a licensed practitioner who is experienced in the use and administration of Nitrogen and is familiar with the indications, effects, dosages, methods, and frequency and duration of administration, and with the hazards, contraindications and side effects, and the precautions to be taken. WARNING: CONTAINS GAS UNDER PRESSURE; MAY EXPLODE IF HEATED. MAY DISPLACE OXYGEN AND CAUSE RAPID SUFFOCATION. Do not handle until all safety precautions have been read and understood. Use and store only outdoor or in a well-ventilated place. Use a back flow preventive device in the piping. Use only with equipment rated for cylinder pressure. Close valve after each use and when empty. Protect from sunlight when ambient temperature exceeds 52 degrees C (125 degrees F). Read and follow the Safety Date Sheet (SDS) before use. FIRST AID: IF INHALED: Remove person to fresh air and keep comfortable for breathing. Get medical advice/attention. CAS 7727-37-9 DO NOT REMOVE THIS PRODUCT LABEL.
SYOXSA
SYOXSA, INC.
6996 COMMERCE AVE. EL PASO, TX 79915
915-771-7674